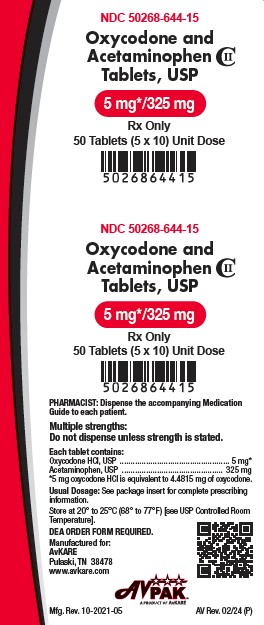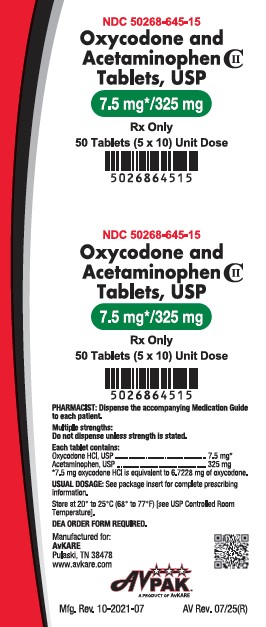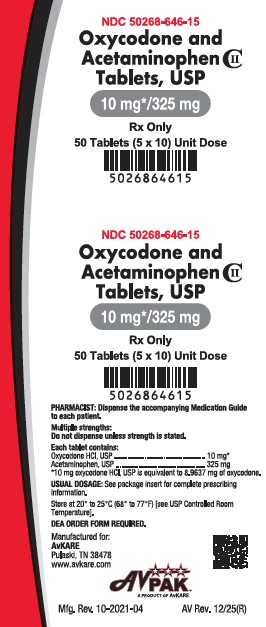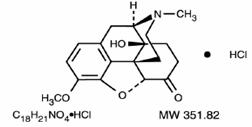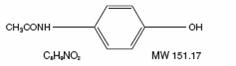 DRUG LABEL: Oxycodone and Acetaminophen
NDC: 50268-646 | Form: TABLET
Manufacturer: AvPAK
Category: prescription | Type: HUMAN PRESCRIPTION DRUG LABEL
Date: 20260121
DEA Schedule: CII

ACTIVE INGREDIENTS: ACETAMINOPHEN 325 mg/1 1; OXYCODONE HYDROCHLORIDE 10 mg/1 1
INACTIVE INGREDIENTS: STARCH, CORN; POVIDONE; CELLULOSE, MICROCRYSTALLINE; STEARIC ACID; CROSPOVIDONE; SILICON DIOXIDE; MAGNESIUM STEARATE

Oxycodone and Acetaminophen Tablets, USP CII
Rx Only

BOXED WARNING

WARNING: ADDICTION, ABUSE, AND MISUSE; RISK EVALUATION AND MITIGATION STRATEGY (REMS); LIFE-THREATENING RESPIRATORY DEPRESSION; ACCIDENTAL INGESTION; NEONATAL OPIOID WITHDRAWAL SYNDROME, CYTOCHROME P450 3A4 INTERACTION; HEPATOTOXICITY, and RISKS FROM CONCOMITANT USE WITH BENZODIAZEPINES OR OTHER CNS DEPRESSANTS

Addiction, Abuse, and Misuse

Oxycodone and Acetaminophen Tablets exposes patients and other users to the risks of opioid addiction, abuse, and misuse, which can lead to overdose and death. Assess each patient’s risk prior to prescribing Oxycodone and Acetaminophen Tablets, and monitor all patients regularly for the development of these behaviors and conditions [see WARNINGS].

Opioid Analgesic Risk Evaluation and Mitigation Strategy (REMS)

To ensure that the benefits of opioid analgesics outweigh the risks of addiction, abuse, and misuse, the Food and Drug Administration (FDA) has required a REMS for these products [see WARNINGS]. Under the requirements of the REMS, drug companies with approved opioid analgesic products must make REMS-compliant education programs available to healthcare providers. Healthcare providers are strongly encouraged to

- complete a REMS-compliant education program.
- counsel patients and/or their caregivers, with every prescription, on safe use, serious risks, storage, and disposal of these products.
- emphasize to patients and their caregivers the importance of reading the Medication Guide every time it is provided by their pharmacist.
- consider other tools to improve patient, household, and community safety.

Life-Threatening Respiratory Depression

Serious, life-threatening, or fatal respiratory depression may occur with use of Oxycodone and Acetaminophen Tablets. Monitor for respiratory depression, especially during initiation of Oxycodone and Acetaminophen Tablets or following a dose increase [see WARNINGS].

Accidental Ingestion

Accidental ingestion of Oxycodone and Acetaminophen Tablets, especially by children, can result in a fatal overdose of Oxycodone and Acetaminophen Tablets [see WARNINGS].

Neonatal Opioid Withdrawal Syndrome

Prolonged use of Oxycodone and Acetaminophen Tablets during pregnancy can result in neonatal opioid withdrawal syndrome, which may be life-threatening if not recognized and treated, and requires management according to protocols developed by neonatology experts. If opioid use is required for a prolonged period in a pregnant woman, advise the patient of the risk of neonatal opioid withdrawal syndrome and ensure that appropriate treatment will be available [see WARNINGS].

Cytochrome P450 3A4 Interaction

The concomitant use of Oxycodone and Acetaminophen Tablets with all cytochrome P450 3A4 inhibitors may result in an increase in oxycodone plasma concentrations, which could increase or prolong adverse reactions and may cause potentially fatal respiratory depression. In addition, discontinuation of a concomitantly used cytochrome P450 3A4 inducer may result in an increase in oxycodone plasma concentrations. Monitor patients receiving Oxycodone and Acetaminophen Tablets and any CYP3A4 inhibitor or inducer [see CLINICAL PHARMACOLOGY, WARNINGS, PRECAUTIONS; Drug Interactions].

Hepatotoxicity

Acetaminophen has been associated with cases of acute liver failure, at times resulting in liver transplant and death. Most of the cases of liver injury are associated with the use of acetaminophen at doses that exceed 4,000 mg per day, and often involve more than one acetaminophen-containing product.

Risks From Concomitant Use With Benzodiazepines Or Other CNS Depressants

Concomitant use of opioids with benzodiazepines or other central nervous system (CNS) depressants, including alcohol, may result in profound sedation, respiratory depression, coma, and death [see WARNINGS, PRECAUTIONS; Drug Interactions].

- Reserve concomitant prescribing of Oxycodone and Acetaminophen Tablets and benzodiazepines or other CNS depressants for use in patients for whom alternative treatment options are inadequate.
- Limit dosages and durations to the minimum required.
- Follow patients for signs and symptoms of respiratory depression and sedation.

DESCRIPTION

Oxycodone and Acetaminophen is available in tablets for oral administration.

Each tablet for oral administration contains:

Oxycodone Hydrochloride USP……………. 5 mg*

(*5 mg Oxycodone Hydrochloride, USP is equivalent to 4.4815 mg Oxycodone)

Acetaminophen USP………………………325 mg

Oxycodone Hydrochloride USP……………. 7.5 mg*
(*7.5 mg Oxycodone Hydrochloride, USP is equivalent to 6.7228 mg Oxycodone)

Acetaminophen USP………………………325 mg

Oxycodone Hydrochloride USP……………. 10 mg*
(*10 mg Oxycodone Hydrochloride, USP is equivalent to 8.9637 mg Oxycodone)
Acetaminophen USP………………………325 mg

Inactive Ingredients

The tablets contain colloidal silicon dioxide, crospovidone, magnesium stearate, microcrystalline cellulose, povidone, pregelatinized starch and stearic acid.

Oxycodone and Acetaminophen Tablets, USP contain oxycodone, 14-hydroxydihydrocodeinone, a semisynthetic opioid analgesic which occurs as a white, odorless, crystalline powder having a saline, bitter taste. The molecular formula for oxycodone hydrochloride is C18H21NO4•HCl and the molecular weight 351.82. It is derived from the opium alkaloid, thebaine, and may be represented by the following structural formula:

Oxycodone and Acetaminophen Tablets, USP contain acetaminophen, USP, 4’-hydroxyacetanilide, is a non-opiate, non-salicylate analgesic and antipyretic which occurs as a white, odorless, crystalline powder, possessing a slightly bitter taste. The molecular formula for acetaminophen is C8H9NO2 and the molecular weight is 151.17. It may be represented by the following structural formula:

CLINICAL PHARMACOLOGY

Mechanism of Action

Oxycodone is a full opioid agonist with relative selectivity for the mu-opioid receptor, although it can interact with other opioid receptors at higher doses. The principal therapeutic action of oxycodone is analgesia. Like all full opioid agonists, there is no ceiling effect for analgesia with oxycodone. Clinically, dosage is titrated to provide adequate analgesia and may be limited by adverse reactions, including respiratory and CNS depression.

The precise mechanism of the analgesic action is unknown. However, specific CNS opioid receptors for endogenous compounds with opioid-like activity have been identified throughout the brain and spinal cord and are thought to play a role in the analgesic effects of this drug.

The precise mechanism of the analgesic properties of acetaminophen is not established but is thought to involve central actions.

Pharmacodynamics

Effects on the Central Nervous System

Oxycodone produces respiratory depression by direct action on brain stem respiratory centers. The respiratory depression involves a reduction in the responsiveness of the brain stem respiratory centers to both increases in carbon dioxide tension and electrical stimulation.

Oxycodone causes miosis, even in total darkness. Pinpoint pupils are a sign of opioid overdose but are not pathognomonic (e.g., pontine lesions of hemorrhagic or ischemic origins may produce similar findings). Marked mydriasis rather than miosis may be seen due to hypoxia in overdose situations.

Therapeutic doses of acetaminophen have negligible effects on the cardiovascular or respiratory systems; however, toxic doses may cause circulatory failure and rapid, shallow breathing.

Effects on the Gastrointestinal Tract and Other Smooth Muscle

Oxycodone causes a reduction in motility associated with an increase in smooth muscle tone in the antrum of the stomach and duodenum. Digestion of food in the small intestine is delayed and propulsive contractions are decreased. Propulsive peristaltic waves in the colon are decreased, while tone may be increased to the point of spasm, resulting in constipation. Other opioid-induced effects may include a reduction in biliary and pancreatic secretions, spasm of sphincter of Oddi, and transient elevations in serum amylase.

Effects on the Cardiovascular System

Oxycodone produces peripheral vasodilation which may result in orthostatic hypotension or syncope. Manifestations of histamine release and/or peripheral vasodilation may include pruritus, flushing, red eyes, sweating, and/or orthostatic hypotension.

Effects on the Endocrine System

Opioids inhibit the secretion of adrenocorticotropic hormone (ACTH), cortisol, and luteinizing hormone (LH) in humans [see ADVERSE REACTIONS]. They also stimulate prolactin, growth hormone (GH) secretion, and pancreatic secretion of insulin and glucagon.

Chronic use of opioids may influence the hypothalamic-pituitary-gonadal axis, leading to androgen deficiency that may manifest as symptoms as low libido, impotence, erectile dysfunction, amenorrhea, or infertility. The causal role of opioids in the syndrome of hypogonadism is unknown because the various medical, physical, lifestyle, and psychological stressors that may influence gonadal hormone levels have not been adequately controlled for in studies conducted to date [see ADVERSE REACTIONS] .

Effects on the Immune System

Opioids have been shown to have a variety of effects on components of the immune system. The clinical significance of these findings is unknown. Overall, the effects of opioids appear to be modestly immunosuppressive.

Concentration–Efficacy Relationships

The minimum effective analgesic concentration will vary widely among patients, especially among patients who have been previously treated with potent agonist opioids. The minimum effective analgesic concentration of oxycodone for any individual patient may increase over time due to an increase in pain, the development of a new pain syndrome, and/or the development of analgesic tolerance [see DOSAGE AND ADMINISTRATION] .

Concentration–Adverse Reaction Relationships

There is a relationship between increasing oxycodone plasma concentration and increasing frequency of dose-related opioid adverse reactions such as nausea, vomiting, CNS effects, and respiratory depression. In opioid-tolerant patients, the situation may be altered by the development of tolerance to opioid-related adverse reactions [see DOSAGE AND ADMINISTRATION] .

Pharmacokinetics

Absorption and Distribution

The mean absolute oral bioavailability of oxycodone in cancer patients was reported to be about 87%. Oxycodone has been shown to be 45% bound to human plasma proteins in vitro. The volume of distribution after intravenous administration is 211.9 ±186.6 L.

Absorption of acetaminophen is rapid and almost complete from the GI tract after oral administration. With overdosage, absorption is complete in 4 hours. Acetaminophen is relatively uniformly distributed throughout most body fluids. Binding of the drug to plasma proteins is variable; only 20% to 50% may be bound at the concentrations encountered during acute intoxication.

Metabolism and Elimination

Oxycodone

In humans, oxycodone is extensively metabolized to noroxycodone by means of CYP3A-mediated N-demethylation, oxymorphone by means of CYP2D6-mediated O-demethylation, and their glucuronides [see PRECAUTIONS; Drug Interactions] .

Acetaminophen

Acetaminophen is rapidly absorbed from the gastrointestinal tract and is distributed throughout most body tissues. A small fraction (10% to 25%) of acetaminophen is bound to plasma proteins. The plasma half-life is 1.25 to 3 hours, but may be increased by liver damage and following overdosage. Elimination of acetaminophen is principally by liver metabolism (conjugation) and subsequent renal excretion of metabolites. Acetaminophen is primarily metabolized in the liver by first-order kinetics and involves three principal separate pathways: conjugation with glucuronide; conjugation with sulfate; and oxidation via the cytochrome, P450-dependent, mixed-function oxidase enzyme pathway to form a reactive intermediate metabolite, which conjugates with glutathione and is then further metabolized to form cysteine and mercapturic acid conjugates. The principal cytochrome P450 isoenzyme involved appears to be CYP2E1, with CYP1A2 and CYP3A4 as additional pathways. Approximately 85% of an oral dose appears in the urine within 24 hours of administration, most as the glucuronide conjugate, with small amounts of other conjugates and unchanged drug [see OVERDOSAGE] for toxicity information.

INDICATIONS AND USAGE

Oxycodone and Acetaminophen Tablets are indicated for the management of pain severe enough to require an opioid analgesic and for which alternative treatments are inadequate.

Limitations of Use

Because of the risks of addiction, abuse, and misuse, with opioids, even at recommended doses [see WARNINGS], reserve Oxycodone and Acetaminophen Tablets for use in patients for whom alternative treatment options [e.g., non-opioid analgesics]

• Have not been tolerated, or are not expected to be tolerated,

• Have not provided adequate analgesia, or are not expected to provide adequate analgesia

CONTRAINDICATIONS

Oxycodone and Acetaminophen Tablets are contraindicated in patients with:

- Significant respiratory depression [see WARNINGS]
- Acute or severe bronchial asthma in an unmonitored setting or in the absence of resuscitative equipment [see WARNINGS]
- Known or suspected gastrointestinal obstruction, including paralytic ileus [see WARNINGS]
- Hypersensitivity to oxycodone, acetaminophen, or any other component of the product (e.g., anaphylaxis) [see WARNINGS, ADVERSE REACTIONS]

WARNINGS

Addiction, Abuse, and Misuse

Oxycodone and Acetaminophen Tablets contain oxycodone, a Schedule II controlled substance. As an opioid, Oxycodone and Acetaminophen Tablets exposes users to the risks of addiction, abuse, and misuse [see DRUG ABUSE AND DEPENDENCE].

Although the risk of addiction in any individual is unknown, it can occur in patients

appropriately prescribed Oxycodone and Acetaminophen Tablets. Addiction can occur at recommended dosages and if the drug is misused or abused.

Assess each patient’s risk for opioid addiction, abuse, or misuse prior to prescribing Oxycodone and Acetaminophen Tablets, and monitor all patients receiving Oxycodone and Acetaminophen Tablets for the development of these behaviors and conditions. Risks are increased in patients with a personal or family history of substance abuse (including drug or alcohol abuse or addiction) or mental illness (e.g., major depression). The potential for these risks should not, however, prevent the proper management of pain in any given patient. Patients at increased risk may be prescribed opioids such as Oxycodone and Acetaminophen Tablets, but use in such patients necessitates intensive counseling about the risks and proper use of Oxycodone and Acetaminophen Tablets along with intensive monitoring for signs of addiction, abuse, and misuse.

Opioids are sought by drug abusers and people with addiction disorders and are subject to criminal diversion. Consider these risks when prescribing or dispensing Oxycodone and Acetaminophen Tablets. Strategies to reduce these risks include prescribing the drug in the smallest appropriate quantity and advising the patient on the proper disposal of unused drug [see PRECAUTIONS; Information for Patients/Caregivers]. Contact local state professional licensing board or state controlled substances authority for information on how to prevent and detect abuse or diversion of this product.

Opioid Analgesic Risk Evaluation and Mitigation Strategy (REMS)

To ensure that the benefits of opioid analgesics outweigh the risks of addiction, abuse, and misuse, the Food and Drug Administration (FDA) has required a Risk Evaluation and Mitigation Strategy (REMS) for these products. Under the requirements of the REMS, drug companies with approved opioid analgesic products must make REMS-compliant education programs available to healthcare providers. Healthcare providers are strongly encouraged to do all of the following:

- Complete a REMS-compliant education program offered by an accredited provider of continuing education (CE) or another education program that includes all the elements of the FDA Education Blueprint for Health Care Providers Involved in the Management or Support of Patients with Pain.
- Discuss the safe use, serious risks, and proper storage and disposal of opioid analgesics with patients and/or their caregivers every time these medicines are prescribed. The Patient Counseling Guide (PCG) can be obtained at this link: www.fda.gov/OpioidAnalgesicREMSPCG.
- Emphasize to patients and their caregivers the importance of reading the Medication Guide that they will receive from their pharmacist every time an opioid analgesic is dispensed to them.
- Consider using other tools to improve patient, household, and community safety, such as patient-prescriber agreements that reinforce patient-prescriber responsibilities.

To obtain further information on the opioid analgesic REMS and for a list of accredited REMS CME/CE, call 800-503-0784, or log on to www.opioidanalgesicrems.com. The FDA Blueprint can be found at www.fda.gov/OpioidAnalgesicREMSBlueprint.

Life-Threatening Respiratory Depression

Serious, life-threatening, or fatal respiratory depression has been reported with the use of opioids, even when used as recommended. Respiratory depression, if not immediately recognized and treated, may lead to respiratory arrest and death. Management of respiratory depression may include close observation, supportive measures, and use of opioid antagonists, depending on the patient’s clinical status [see OVERDOSAGE]. Carbon dioxide (CO2) retention from opioid-induced respiratory depression can exacerbate the sedating effects of opioids.

While serious, life-threatening, or fatal respiratory depression can occur at any time during the use of Oxycodone and Acetaminophen Tablets, the risk is greatest during the initiation of therapy or following a dosage increase. Monitor patients closely for respiratory depression, especially within the first 24 to 72 hours of initiating therapy with and following dosage increases of Oxycodone and Acetaminophen Tablets.

To reduce the risk of respiratory depression, proper dosing and titration of Oxycodone and Acetaminophen Tablets are essential [see DOSAGE AND ADMINISTRATION]. Overestimating the Oxycodone and Acetaminophen Tablets dosage when converting patients from another opioid product can result in a fatal overdose with the first dose.

Accidental ingestion of Oxycodone and Acetaminophen Tablets, especially by children, can result in respiratory depression and death due to an overdose of Oxycodone and Acetaminophen Tablets.

Neonatal Opioid Withdrawal Syndrome

Prolonged use of Oxycodone and Acetaminophen Tablets during pregnancy can result in withdrawal in the neonate. Neonatal opioid withdrawal syndrome, unlike opioid withdrawal syndrome in adults, may be life-threatening if not recognized and treated, and requires management according to protocols developed by neonatology experts. Observe newborns for signs of neonatal opioid withdrawal syndrome and manage accordingly. Advise pregnant women using opioids for a prolonged period of the risk of neonatal opioid withdrawal syndrome and ensure that appropriate treatment will be available [see PRECAUTIONS; Information for Patients/Caregivers, Pregnancy] .

Risks of Concomitant Use or Discontinuation of Cytochrome P450 3A4 Inhibitors and Inducers

Concomitant use of Oxycodone and Acetaminophen Tablets with a CYP3A4 inhibitor, such as macrolide antibiotics (e.g., erythromycin), azole-antifungal agents (e.g., ketoconazole), and protease inhibitors (e.g., ritonavir), may increase plasma concentrations of oxycodone hydrochloride and prolong opioid adverse reactions, which may cause potentially fatal respiratory depression [see WARNINGS], particularly when an inhibitor is added after a stable dose of Oxycodone and Acetaminophen Tablets is achieved. Similarly, discontinuation of a CYP3A4 inducer, such as rifampin, carbamazepine, and phenytoin, in Oxycodone and Acetaminophen Tablets-treated patients may increase oxycodone plasma concentrations and prolong opioid adverse reactions. When using Oxycodone and Acetaminophen Tablets with CYP3A4 inhibitors or discontinuing CYP3A4 inducers in Oxycodone and Acetaminophen Tablets-treated patients, monitor patients closely at frequent intervals and consider dosage reduction of Oxycodone and Acetaminophen Tablets until stable drug effects are achieved [see PRECAUTIONS; Drug Interactions].

Concomitant use of Oxycodone and Acetaminophen Tablets with CYP3A4 inducers or discontinuation of an CYP3A4 inhibitor could decrease oxycodone hydrochloride plasma concentrations, decrease opioid efficacy or, possibly, lead to a withdrawal syndrome in a patient who had developed physical dependence to oxycodone hydrochloride. When using Oxycodone and Acetaminophen Tablets with CYP3A4 inducers or discontinuing CYP3A4 inhibitors, monitor patients closely at frequent intervals and consider increasing the opioid dosage if needed to maintain adequate analgesia or if symptoms of opioid withdrawal occur [see PRECAUTIONS; Drug Interactions].

Risks from Concomitant Use with Benzodiazepines or Other CNS Depressants

Profound sedation, respiratory depression, coma, and death may result from the concomitant use of Oxycodone and Acetaminophen Tablets with benzodiazepines or other CNS depressants (e.g., non-benzodiazepine sedatives/hypnotics, anxiolytics, tranquilizers, muscle relaxants, general anesthetics, antipsychotics, other opioids, alcohol). Because of these risks, reserve concomitant prescribing of these drugs for use in patients for whom alternative treatment options are inadequate.

Observational studies have demonstrated that concomitant use of opioid analgesics and benzodiazepines increases the risk of drug-related mortality compared to use of opioid analgesics alone. Because of similar pharmacological properties, it is reasonable to expect similar risk with the concomitant use of other CNS depressant drugs with opioid analgesics [see PRECAUTIONS; Drug Interactions].

If the decision is made to prescribe a benzodiazepine or other CNS depressant concomitantly with an opioid analgesic, prescribe the lowest effective dosages and minimum durations of concomitant use. In patients already receiving an opioid analgesic, prescribe a lower initial dose of the benzodiazepine or other CNS depressant than indicated in the absence of an opioid, and titrate based on clinical response. If an opioid analgesic is initiated in a patient already taking a benzodiazepine or other CNS depressant, prescribe a lower initial dose of the opioid analgesic, and titrate based on clinical response. Follow patients closely for signs and symptoms of respiratory depression and sedation.

Advise both patients and caregivers about the risks of respiratory depression and sedation when Oxycodone and Acetaminophen Tablets are used with benzodiazepines or other CNS depressants (including alcohol and illicit drugs). Advise patients not to drive or operate heavy machinery until the effects of concomitant use of the benzodiazepine or other CNS depressant have been determined. Screen patients for risk of substance use disorders, including opioid abuse and misuse, and warn them of the risk for overdose and death associated with the use of additional CNS depressants including alcohol and illicit drugs.

Life-Threatening Respiratory Depression in Patients with Chronic Pulmonary Disease or in Elderly, Cachectic, or Debilitated Patients

The use of Oxycodone and Acetaminophen Tablets in patients with acute or severe bronchial asthma in an unmonitored setting or in the absence of resuscitative equipment is contraindicated.

Patients with Chronic Pulmonary Disease: Oxycodone and Acetaminophen Tablets-treated patients with significant chronic obstructive pulmonary disease or cor pulmonale, and those with a substantially decreased respiratory reserve, hypoxia, hypercapnia, or pre-existing respiratory depression are at increased risk of decreased respiratory drive including apnea, even at recommended dosages of Oxycodone and Acetaminophen Tablets [see WARNINGS; Life- Threatening Respiratory Depression].

Elderly, Cachetic, or Debilitated Patients: Life-threatening respiratory depression is more likely to occur in elderly, cachectic, or debilitated patients because they may have altered pharmacokinetics or altered clearance compared to younger, healthier patients [see WARNINGS; Life-Threatening Respiratory Depression].

Monitor such patients closely, particularly when initiating and titrating Oxycodone and Acetaminophen Tablets and when Oxycodone and Acetaminophen Tablets are given concomitantly with other drugs that depress respiration [see WARNINGS; Life-Threatening Respiratory Depression]. Alternatively, consider the use of non-opioid analgesics in these patients.

Adrenal Insufficiency

Cases of adrenal insufficiency have been reported with opioid use, more often following greater than one month of use. Presentation of adrenal insufficiency may include non-specific symptoms and signs including nausea, vomiting, anorexia, fatigue, weakness, dizziness, and low blood pressure. If adrenal insufficiency is suspected, confirm the diagnosis with diagnostic testing as soon as possible. If adrenal insufficiency is diagnosed, treat with physiologic replacement doses of corticosteroids. Wean the patient off of the opioid to allow adrenal function to recover and continue corticosteroid treatment until adrenal function recovers. Other opioids may be tried as some cases reported use of a different opioid without recurrence of adrenal insufficiency. The information available does not identify any particular opioids as being more likely to be associated with adrenal insufficiency.

Severe Hypotension

Oxycodone and Acetaminophen Tablets may cause severe hypotension including orthostatic hypotension and syncope in ambulatory patients. There is increased risk in patients whose ability to maintain blood pressure has already been compromised by a reduced blood volume or concurrent administration of certain CNS depressant drugs (e.g., phenothiazines or general anesthetics) [see PRECAUTIONS; Drug Interactions]. Monitor these patients for signs of hypotension after initiating or titrating the dosage of Oxycodone and Acetaminophen Tablets. In patients with circulatory shock Oxycodone and Acetaminophen Tablets may cause vasodilatation that can further reduce cardiac output and blood pressure. Avoid the use of Oxycodone and Acetaminophen Tablets with circulatory shock.

Hepatotoxicity

Acetaminophen has been associated with cases of acute liver failure, at times resulting in liver transplant and death. Most of the cases of liver injury are associated with the use of acetaminophen at doses that exceed 4,000 milligrams per day, and often involve more than one acetaminophen-containing product. The excessive intake of acetaminophen may be intentional to cause self-harm or unintentional as patients attempt to obtain more pain relief or unknowingly take other acetaminophen-containing products.

The risk of acute liver failure is higher in individuals with underlying liver disease and in individuals who ingest alcohol while taking acetaminophen.

Instruct patients to look for acetaminophen or APAP on package labels and not to use more than one product that contains acetaminophen. Instruct patients to seek medical attention immediately upon ingestion of more than 4,000 milligrams of acetaminophen per day, even if they feel well.

Serious Skin Reactions

Rarely, acetaminophen may cause serious skin reactions such as acute generalized exanthematous pustulosis (AGEP), Stevens-Johnson Syndrome (SJS), and toxic epidermal necrolysis (TEN), which can be fatal. Patients should be informed about the signs of serious skin reactions, and use of the drug should be discontinued at the first appearance of skin rash or any other sign of hypersensitivity.

Hypersensitivity/Anaphylaxis

There have been post-marketing reports of hypersensitivity and anaphylaxis associated with use of acetaminophen. Clinical signs included swelling of the face, mouth, and throat, respiratory distress, urticaria, rash, pruritus, and vomiting. There were infrequent reports of life-threatening anaphylaxis requiring emergency medical attention. Instruct patients to discontinue Oxycodone and Acetaminophen Tablets immediately and seek medical care if they experience these symptoms. Do not prescribe Oxycodone and Acetaminophen Tablets for patients with acetaminophen allergy [see PRECAUTIONS; Information for Patients/Caregivers].

Risks of Use in Patients with Increased Intracranial Pressure, Brain Tumors, Head Injury, or Impaired Consciousness

In patients who may be susceptible to the intracranial effects of CO2 retention (e.g., those with evidence of increased intracranial pressure or brain tumors), Oxycodone and Acetaminophen Tablets may reduce respiratory drive, and the resultant CO2 retention can further increase intracranial pressure. Monitor such patients for signs of sedation and respiratory depression, particularly when initiating therapy with Oxycodone and Acetaminophen Tablets.

Opioids may also obscure the clinical course in a patient with a head injury. Avoid the use of Oxycodone and Acetaminophen Tablets in patients with impaired consciousness or coma.

Risks of Use in Patients with Gastrointestinal Conditions

Oxycodone and Acetaminophen Tablets are contraindicated in patients with known or suspected gastrointestinal obstruction, including paralytic ileus.

The administration of Oxycodone and Acetaminophen Tablets, or other opioids may obscure the diagnosis or clinical course in patients with acute abdominal conditions.

The oxycodone in Oxycodone and Acetaminophen Tablets may cause spasm of the sphincter of Oddi. Opioids may cause increases in serum amylase. Monitor patients with biliary tract disease, including acute pancreatitis, for worsening symptoms.

Increased Risk of Seizures in Patients with Seizure Disorders

The oxycodone in Oxycodone and Acetaminophen Tablets may increase the frequency of seizures in patients with seizure disorders, and may increase the risk of seizures occurring in other clinical settings associated with seizures. Monitor patients with a history of seizure disorders for worsened seizure control during Oxycodone and Acetaminophen Tablets therapy.

Withdrawal

Avoid the use of mixed agonist/antagonist (e.g., pentazocine, nalbuphine, and butorphanol) or partial agonist (e.g., buprenorphine) analgesics in patients who are receiving a full opioid agonist analgesic, including Oxycodone and Acetaminophen Tablets. In these patients, mixed agonist/antagonist and partial analgesics may reduce the analgesic effect and/or precipitate withdrawal symptoms.

When discontinuing Oxycodone and Acetaminophen Tablets, gradually taper the dosage [see DOSAGE AND ADMINISTRATION]. Do not abruptly discontinue Oxycodone and Acetaminophen Tablets [see DRUG ABUSE AND DEPENDENCE].

Risks of Driving and Operating Machinery

Oxycodone and Acetaminophen Tablets may impair the mental or physical abilities needed to perform potentially hazardous activities such as driving a car or operating machinery. Warn patients not to drive or operate dangerous machinery unless they are tolerant to the effects of Oxycodone and Acetaminophen Tablets and know how they will react to the medication [see PRECAUTIONS; Information for Patients/Caregivers].

PRECAUTIONS

Information for Patients/Caregivers

Advise the patient to read the FDA-approved patient labeling (Medication Guide).

Addiction, Abuse, and Misuse

Inform patients that the use of Oxycodone and Acetaminophen Tablets, even when taken as recommended, can result in addiction, abuse, and misuse, which can lead to overdose and death [see WARNINGS]. Instruct patients not to share Oxycodone and Acetaminophen Tablets with others and to take steps to protect Oxycodone and Acetaminophen Tablets from theft or misuse.

Life-Threatening Respiratory Depression

Inform patients of the risk of life-threatening respiratory depression, including information that the risk is greatest when starting Oxycodone and Acetaminophen Tablets or when the dosage is increased, and that it can occur even at recommended dosages [see WARNINGS]. Advise patients how to recognize respiratory depression and to seek medical attention if breathing difficulties develop.

Accidental Ingestion

Inform patients that accidental ingestion, especially by children, may result in respiratory depression or death [see WARNINGS]. Instruct patients to take steps to store Oxycodone and Acetaminophen Tablets securely and to dispose of unused Oxycodone and Acetaminophen Tablets by flushing tablets down the toilet. In the case of accidental ingestions, emergency medical care should be sought immediately.

Interactions with Benzodiazepines and Other CNS Depressants

Inform patients and caregivers that potentially fatal additive effects may occur if Oxycodone and Acetaminophen Tablets are used with benzodiazepines and other CNS depressants, including alcohol, and not to use these concomitantly unless supervised by a health care provider [see WARNINGS, PRECAUTIONS; Drug Interactions].

Serotonin Syndrome

Inform patients that opioids could cause a rare but potentially life-threatening condition resulting from concomitant administration of serotonergic drugs. Warn patients of the symptoms of serotonin syndrome and to seek medical attention right away if symptoms develop. Instruct patients to inform their healthcare providers if they are taking, or plan to take serotonergic medications [see PRECAUTIONS; Drug Interactions].

Monoamine Oxidase Inhibitor (MAOI) Interaction

Inform patients to avoid taking Oxycodone and Acetaminophen Tablets while using any drugs that inhibit monoamine oxidase. Patients should not start MAOIs while taking Oxycodone and Acetaminophen Tablets [see PRECAUTIONS; Drug Interactions].

Adrenal Insufficiency

Inform patients that opioids could cause adrenal insufficiency, a potentially life-threatening condition. Adrenal insufficiency may present with non-specific symptoms and signs such as nausea, vomiting, anorexia, fatigue, weakness, dizziness, and low blood pressure. Advise patients to seek medical attention if they experience a constellation of these symptoms [see WARNINGS].

Important Administration Instructions

Instruct patients how to properly take Oxycodone and Acetaminophen Tablets [see DOSAGE AND ADMINISTRATION, WARNINGS].

Advise patients not to adjust the medication dose themselves and to consult with their healthcare provider prior to any dosage adjustment.

Advise patients who are treated with Oxycodone and Acetaminophen Tablets for more than a few weeks not to abruptly discontinue the medication. Advise patients to consult with their physician for a gradual discontinuation dose schedule to taper off the medication.

Maximum Daily Dose of Acetaminophen

Inform patients to not take more than 4,000 milligrams of acetaminophen per day. Advise patients to call their prescriber if they take more than the recommended dose.

Hypotension

Inform patients that Oxycodone and Acetaminophen Tablets may cause orthostatic hypotension and syncope. Instruct patients how to recognize symptoms of low blood pressure and how to reduce the risk of serious consequences should hypotension occur (e.g., sit or lie down, carefully rise from a sitting or lying position) [see WARNINGS].

Anaphylaxis

Inform patients that anaphylaxis have been reported with ingredients contained in Oxycodone and Acetaminophen Tablets. Advise patients how to recognize such a reaction and when to seek medical attention [see CONTRAINDICATIONS, ADVERSE REACTIONS].

Pregnancy

Neonatal Opioid Withdrawal Syndrome

Inform female patients of reproductive potential that prolonged use of Oxycodone and Acetaminophen Tablets during pregnancy can result in neonatal opioid withdrawal syndrome, which may be life-threatening if not recognized and treated [see WARNINGS, PRECAUTIONS; Pregnancy].

Embryo-Fetal Toxicity

Inform female patients of reproductive potential that Oxycodone and Acetaminophen Tablets can cause fetal harm and to inform the healthcare provider of a known or suspected pregnancy [see PRECAUTIONS; Pregnancy].

Lactation

Advise nursing mothers to monitor infants for increased sleepiness (more than usual), breathing difficulties, or limpness. Instruct nursing mothers to seek immediate medical care if they notice these signs [see PRECAUTIONS; Nursing Mothers].

Infertility

Inform patients that chronic use of opioids may cause reduced fertility. It is not known whether these effects on fertility are reversible [see ADVERSE REACTIONS].

Driving or Operating Heavy Machinery

Inform patients that Oxycodone and Acetaminophen Tablets may impair the ability to perform potentially hazardous activities such as driving a car or operating heavy machinery. Advise patients not to perform such tasks until they know how they will react to the medication [see PRECAUTIONS].

Constipation

Advise patients of the potential for severe constipation, including management instructions and when to seek medical attention [see ADVERSE REACTIONS, CLINICAL PHARMACOLOGY].

Disposal of Unused Oxycodone and Acetaminophen Tablets

Advise patients to dispose of unused Oxycodone and Acetaminophen Tablets by flushing unused tablets down the toilet.

Laboratory Tests

Although oxycodone may cross-react with some drug urine tests, no available studies were found which determined the duration of detectability of oxycodone in urine drug screens. However, based on pharmacokinetic data, the approximate duration of detectability for a single dose of oxycodone is roughly estimated to be one to two days following drug exposure.

Urine testing for opiates may be performed to determine illicit drug use and for medical reasons such as evaluation of patients with altered states of consciousness or monitoring efficacy of drug rehabilitation efforts. The preliminary identification of opiates in urine involves the use of an immunoassay screening and thin-layer chromatography (TLC). Gas chromatography/mass spectrometry (GC/MS) may be utilized as a third-stage identification step in the medical investigational sequence for opiate testing after immunoassay and TLC. The identities of 6-keto opiates (e.g., oxycodone) can further be differentiated by the analysis of their methoximetrimethylsilyl (MO-TMS) derivative.

Drug Interactions

Inhibitors of CYP3A4 and CYP2D6

The concomitant use of Oxycodone and Acetaminophen Tablets and CYP3A4 inhibitors, such as macrolide antibiotics (e.g., erythromycin), azole-antifungal agents (e.g. ketoconazole), and protease inhibitors (e.g., ritonavir), can increase the plasma concentration of oxycodone, resulting in increased or prolonged opioid effects. These effects could be more pronounced with concomitant use of Oxycodone and Acetaminophen Tablets and CYP3A4 and CYP2D6 inhibitors, particularly when an inhibitor is added after a stable dose of Oxycodone and Acetaminophen Tablets is achieved [see WARNINGS].

After stopping a CYP3A4 inhibitor, as the effects of the inhibitor decline, the oxycodone plasma concentration will decrease [see CLINICAL PHARMACOLOGY], resulting in decreased opioid efficacy or a withdrawal syndrome in patients who had developed physical dependence to Oxycodone and Acetaminophen Tablets.

If concomitant use is necessary, consider dosage reduction of Oxycodone and Acetaminophen Tablets until stable drug effects are achieved. Monitor patients for respiratory depression and sedation at frequent intervals. If a CYP3A4 inhibitor is discontinued, consider increasing the Oxycodone and Acetaminophen Tablets dosage until stable drug effects are achieved. Monitor for signs of opioid withdrawal.

Inducers of CYP3A4

The concomitant use of Oxycodone and Acetaminophen Tablets and CYP3A4 inducers, such as rifampin, carbamazepine, and phenytoin, can decrease the plasma concentration of oxycodone [see CLINICAL PHARMACOLOGY], resulting in decreased efficacy or onset of a withdrawal syndrome in patients who have developed physical dependence to Oxycodone and Acetaminophen Tablets [see WARNINGS].

After stopping a CYP3A4 inducer, as the effects of the inducer decline, the oxycodone plasma concentration will increase [see CLINICAL PHARMACOLOGY], which could increase or prolong both the therapeutic effects and adverse reactions, and may cause serious respiratory depression.

If concomitant use is necessary, consider increasing the Oxycodone and Acetaminophen Tablets dosage until stable drug effects are achieved. Monitor for signs of opioid withdrawal. If a CYP3A4 inducer is discontinued, consider Oxycodone and Acetaminophen Tablets dosage reduction and monitor for signs of respiratory depression.

Benzodiazepines and Other CNS Depressants

Due to additive pharmacologic effect, the concomitant use of benzodiazepines and other CNS depressants such as benzodiazepines and other sedative hypnotics, anxiolytics, tranquilizers, muscle relaxants, general anesthetics, antipsychotics, and other opioids, including alcohol, can increase the risk of hypotension, respiratory depression, profound sedation, coma, and death.

Reserve concomitant prescribing of these drugs for use in patients for whom alternative treatment options are inadequate. Limit dosages and durations to the minimum required. Follow patients closely for signs of respiratory depression and sedation [see WARNINGS].

Serotonergic Drugs

The concomitant use of opioids with other drugs that affect the serotonergic neurotransmitter system, such as selective serotonin reuptake inhibitors (SSRIs), serotonin and norepinephrine reuptake inhibitors (SNRIs), tricyclic antidepressants (TCAs), tryptans, 5-HT3 receptor antagonists, drugs that affect the serotonin neurotransmitter system (e.g., mirtazapine, trazodone, tramadol), and monoamine oxidase (MAO) inhibitors (those intended to treat psychiatric disorders and also others, such as linezolid and intravenous methylene blue), has resulted in serotonin syndrome [see PRECAUTIONS; Information for Patients/Caregivers].

If concomitant use is warranted, carefully observe the patient, particularly during treatment initiation and dose adjustment. Discontinue Oxycodone and Acetaminophen Tablets if serotonin syndrome is suspected.

Monoamine Oxidase Inhibitors (MAOIs)

The concomitant use of opioids and MAOIs, such as phenelzine, tranylcypromine, linezolid, may manifest as serotonin syndrome or opioid toxicity (e.g., respiratory depression, coma) [see WARNINGS].

The use of Oxycodone and Acetaminophen Tablets is not recommended for patients taking MAOIs or within 14 days of stopping such treatment.

If urgent use of an opioid is necessary, use test doses and frequent titration of small doses to treat pain while closely monitoring blood pressure and signs and symptoms of CNS and respiratory depression.

Mixed Agonist/Antagonist and Partial Agonist Opioid Analgesics

The concomitant use of opioids with other opioid analgesics, such as butorphanol, nalbuphine, pentazocine, may reduce the analgesic effect of Oxycodone and Acetaminophen Tablets and/or precipitate withdrawal symptoms.

Advise patient to avoid concomitant use of these drugs.

Muscle Relaxants

Oxycodone and Acetaminophen Tablets may enhance the neuromuscular-blocking action of skeletal muscle relaxants and produce an increase in the degree of respiratory depression.

If concomitant use is warranted, monitor patients for signs of respiratory depression that may be greater than otherwise expected and decrease the dosage of Oxycodone and Acetaminophen Tablets and/or the muscle relaxant as necessary.

Diuretics

Opioids can reduce the efficacy of diuretics by inducing the release of antidiuretic hormone.

If concomitant use is warranted, monitor patients for signs of diminished diuresis and/or effects on blood pressure and increase the dosage of the diuretic as needed.

Anticholinergic Drugs

The concomitant use of anticholinergic drugs may increase risk of urinary retention and/or severe constipation, which may lead to paralytic ileus.

If concomitant use is warranted, monitor patients for signs of urinary retention or reduced gastric motility when Oxycodone and Acetaminophen Tablets are used concomitantly with anticholinergic drugs.

Alcohol, ethyl

Hepatotoxicity has occurred in chronic alcoholics following various dose levels (moderate to excessive) of acetaminophen.

Oral Contraceptives

Increase in glucuronidation resulting in increased plasma clearance and a decreased half-life of acetaminophen.

Charcoal (activated)

Reduces acetaminophen absorption when administered as soon as possible after overdose.

Beta Blockers (Propranolol)

Propranolol appears to inhibit the enzyme systems responsible for the glucuronidation and oxidation of acetaminophen. Therefore, the pharmacologic effects of acetaminophen may be increased.

Loop Diuretics

The effects of the loop diuretic may be decreased because acetaminophen may decrease renal prostaglandin excretion and decrease plasma renin activity.

Lamotrigine

Serum lamotrigine concentrations may be reduced, producing a decrease in therapeutic effects.

Probenecid

Probenecid may increase the therapeutic effectiveness of acetaminophen slightly.

Zidovudine

The pharmacologic effects of zidovudine may be decreased because of enhanced non-hepatic or renal clearance of zidovudine.

Drug/Laboratory Test Interactions

Depending on the sensitivity/specificity and the test methodology, the individual components of Oxycodone and Acetaminophen Tablets may cross-react with assays used in the preliminary detection of cocaine (primary urinary metabolite, benzoylecgonine) or marijuana (cannabinoids) in human urine. A more specific alternate chemical method must be used in order to obtain a confirmed analytical result. The preferred confirmatory method is gas chromatography/mass spectrometry (GC/MS). Moreover, clinical considerations and professional judgment should be applied to any drug-of-abuse test result, particularly when preliminary positive results are used.

Acetaminophen may interfere with home blood glucose measurement systems; decreases of >20% in mean glucose values may be noted. This effect appears to be drug, concentration and system dependent.

Carcinogenesis, Mutagenesis, Impairment of Fertility

Carcinogenesis

Long-term studies to evaluate the carcinogenic potential of the combination of Oxycodone and Acetaminophen have not been conducted.

Long-term studies in mice and rats have been completed by the National Toxicology Program to evaluate the carcinogenic potential of acetaminophen. In 2-year feeding studies, F344/N rats and B6C3F1 mice were fed a diet containing acetaminophen up to 6,000 ppm. Female rats demonstrated equivocal evidence of carcinogenic activity based on increased incidences of mononuclear cell leukemia at 0.8 times the maximum human daily dose (MHDD) of 4 grams/day, based on a body surface area comparison. In contrast, there was no evidence of carcinogenic activity in male rats that received up to 0.7 times or mice at up to 1.2 to 1.4 times the MHDD, based on a body surface area comparison.

Mutagenesis

The combination of Oxycodone and Acetaminophen has not been evaluated for mutagenicity. Oxycodone alone was negative in a bacterial reverse mutation assay (Ames), an in vitro chromosome aberration assay with human lymphocytes without metabolic activation and an in vivo mouse micronucleus assay. Oxycodone was clastogenic in the human lymphocyte chromosomal assay in the presence of metabolic activation and in the mouse lymphoma assay with or without metabolic activation.

In the published literature, acetaminophen has been reported to be clastogenic when administered at 1,500 mg/kg/day to the rat model (3.6-times the MHDD, based on a body surface area comparison). In contrast, no clastogenicity was noted at a dose of 750 mg/kg/day (1.8-times the MHDD, based on a body surface area comparison), suggesting a threshold effect.

Impairment of Fertility

In studies conducted by the National Toxicology Program, fertility assessments with acetaminophen have been completed in Swiss CD-1 mice via a continuous breeding study. There were no effects on fertility parameters in mice consuming up to 1.7 times the MHDD of acetaminophen, based on a body surface area comparison. Although there was no effect on sperm motility or sperm density in the epididymis, there was a significant increase in the percentage of abnormal sperm in mice consuming 1.78 times the MHDD (based on a body surface comparison) and there was a reduction in the number of mating pairs producing a fifth litter at this dose, suggesting the potential for cumulative toxicity with chronic administration of acetaminophen near the upper limit of daily dosing.

Published studies in rodents report that oral acetaminophen treatment of male animals at doses that are 1.2 times the MHDD and greater (based on a body surface comparison) result in decreased testicular weights, reduced spermatogenesis, reduced fertility, and reduced implantation sites in females given the same doses. These effects appear to increase with the duration of treatment. The clinical significance of these findings is not known.

Infertility

Chronic use of opioids may cause reduced fertility in females and males of reproductive potential. It is not known whether these effects on fertility are reversible [see ADVERSE REACTIONS].

Pregnancy

Teratogenic Effects

Pregnancy Category C

Animal reproductive studies have not been conducted with Oxycodone and Acetaminophen Tablets. It is also not known whether Oxycodone and Acetaminophen Tablets can cause fetal harm when administered to a pregnant woman or can affect reproductive capacity. Oxycodone and Acetaminophen Tablets should not be given to a pregnant woman unless in the judgment of the physician, the potential benefits outweigh the possible hazards.

Nonteratogenic Effects

Fetal/Neonatal Adverse Reactions

Prolonged use of opioid analgesics during pregnancy for medical or nonmedical purposes can result in physical dependence in the neonate and neonatal opioid withdrawal syndrome shortly after birth.

Neonatal opioid withdrawal syndrome presents as irritability, hyperactivity and abnormal sleep pattern, high pitched cry, tremor, vomiting, diarrhea and failure to gain weight. The onset, duration, and severity of neonatal opioid withdrawal syndrome vary based on the specific opioid used, duration of use, timing and amount of last maternal use, and rate of elimination of the drug by the newborn. Observe newborns for symptoms of neonatal opioid withdrawal syndrome and manage accordingly [see WARNINGS].

Labor or Delivery

Opioids cross the placenta and may produce respiratory depression and psycho-physiologic effects in neonates. An opioid antagonist, such as naloxone, must be available for reversal of opioid-induced respiratory depression in the neonate. Oxycodone and Acetaminophen Tablets are not recommended for use in pregnant women during or immediately prior to labor, when other analgesic techniques are more appropriate. Opioid analgesics, including Oxycodone and Acetaminophen Tablets, can prolong labor through actions which temporarily reduce the strength, duration, and frequency of uterine contractions. However, this effect is not consistent and may be offset by an increased rate of cervical dilation, which tends to shorten labor. Monitor neonates exposed to opioid analgesics during labor for signs of excess sedation and respiratory depression.

Nursing Mothers

Ordinarily, nursing should not be undertaken while a patient is receiving Oxycodone and Acetaminophen Tablets because of the possibility of sedation and/or respiratory depression in the infant. Oxycodone is excreted in breast milk in low concentrations, and there have been rare reports of somnolence and lethargy in babies of nursing mothers taking an oxycodone/acetaminophen product. Acetaminophen is also excreted in breast milk in low concentrations.

The developmental and health benefits of breastfeeding should be considered along with the mother’s clinical need for Oxycodone and Acetaminophen Tablets and any potential adverse effects on the breastfed infant from Oxycodone and Acetaminophen Tablets or from the underlying maternal condition.

Infants exposed to Oxycodone and Acetaminophen Tablets through breast milk should be monitored for excess sedation and respiratory depression. Withdrawal symptoms can occur in breastfed infants when maternal administration of an opioid analgesic is stopped, or when breast-feeding is stopped.

Pediatric Use

Safety and effectiveness of Oxycodone and Acetaminophen Tablets in pediatric patients have not been established.

Geriatric Use

Elderly patients (aged 65 years or older) may have increased sensitivity Oxycodone and Acetaminophen Tablets. In general, use caution when selecting a dosage for an elderly patient, usually starting at the low end of the dosing range, reflecting the greater frequency of decreased hepatic, renal, or cardiac function and of concomitant disease or other drug therapy.

Respiratory depression is the chief risk for elderly patients treated with opioids, and has occurred after large initial doses were administered to patients who were not opioid-tolerant or when opioids were co-administered with other agents that depress respiration. Titrate the dosage of Oxycodone and Acetaminophen Tablets slowly in geriatric patients and monitor closely for signs of central nervous system and respiratory depression [see WARNINGS].

These drugs are known to be substantially excreted by the kidney, and the risk of adverse reactions to this drug may be greater in patients with impaired renal function. Because elderly patients are more likely to have decreased renal function, care should be taken in dose selection, and it may be useful to monitor renal function.

Hepatic Impairment

In a pharmacokinetic study of oxycodone in patients with end-stage liver disease, oxycodone plasma clearance decreased and the elimination half-life increased.

Because oxycodone is extensively metabolized in the liver, its clearance may decrease in patients with hepatic impairment. Initiate therapy in these patients with a lower than usual dosage of Oxycodone and Acetaminophen Tablets and titrate carefully. Monitor closely for adverse events such as respiratory depression, sedation, and hypotension [see CLINICAL PHARMACOLOGY].

Renal Impairment

In a study of patients with end stage renal impairment, mean elimination half-life was prolonged in uremic patients due to increased volume of distribution and reduced clearance. Oxycodone should be used with caution in patients with renal impairment.

Because oxycodone is known to be substantially excreted by the kidney, its clearance may decrease in patients with renal impairment. Initiate therapy with a lower than usual dosage of Oxycodone and Acetaminophen Tablets and titrate carefully. Monitor closely for adverse events such as respiratory depression, sedation, and hypotension [see CLINICAL PHARMACOLOGY].

ADVERSE REACTIONS

The following adverse reactions have been identified during post approval use of Oxycodone and Acetaminophen Tablets. Because these reactions are reported voluntarily from a population of uncertain size, it is not always possible to reliably estimate their frequency or establish a causal relationship to drug exposure.

Serious adverse reactions that may be associated with oxycodone and acetaminophen use include respiratory depression, apnea, respiratory arrest, circulatory depression, hypotension, and shock [see OVERDOSAGE].

The most frequently observed non-serious adverse reactions include lightheadedness, dizziness, drowsiness or sedation, nausea, and vomiting. These effects seem to be more prominent in ambulatory than in nonambulatory patients, and some of these adverse reactions may be alleviated if the patient lies down. Other adverse reactions include euphoria, dysphoria, constipation, and pruritus.

Hypersensitivity reactions may include: Skin eruptions, urticarial, erythematous skin reactions. Hematologic reactions may include: thrombocytopenia, neutropenia, pancytopenia, hemolytic anemia. Rare cases of agranulocytosis has likewise been associated with acetaminophen use. In high doses, the most serious adverse effect is a dose-dependent, potentially fatal hepatic necrosis. Renal tubular necrosis and hypoglycemic coma also may occur.

Other adverse reactions obtained from postmarketing experiences with oxycodone and acetaminophen are listed by organ system and in decreasing order of severity and/or frequency as follows:

Body as a Whole: Anaphylactoid reaction, allergic reaction, malaise, asthenia, fatigue, chest pain, fever, hypothermia, thirst, headache, increased sweating, accidental overdose, non-accidental overdose

Cardiovascular: Hypotension, hypertension, tachycardia, orthostatic hypotension, bradycardia, palpitations, dysrhythmias

Central and Peripheral Nervous System:Stupor, tremor, paraesthesia, hypoaesthesia, lethargy, seizures, anxiety, mental impairment, agitation, cerebral edema, confusion, dizziness

Fluid and Electrolyte: Dehydration, hyperkalemia, metabolic acidosis, respiratory alkalosis

Gastrointestinal: Dyspepsia, taste disturbances, abdominal pain, abdominal distention, sweating increased, diarrhea, dry mouth, flatulence, gastrointestinal disorder, nausea, vomiting, pancreatitis, intestinal obstruction, ileus

Hepatic:Transient elevations of hepatic enzymes, increase in bilirubin, hepatitis, hepatic failure, jaundice, hepatotoxicity, hepatic disorder

Hearing and Vestibular: Hearing loss, tinnitus

Hematologic:Thrombocytopenia

Hypersensitivity: Acute anaphylaxis, angioedema, asthma, bronchospasm, laryngeal edema, urticaria, anaphylactoid reaction

Metabolic and Nutritional: Hypoglycemia, hyperglycemia, acidosis, alkalosis

Musculoskeletal: Myalgia, rhabdomyolysis

Ocular: Miosis, visual disturbances, red eye

Psychiatric: Drug dependence, drug abuse, insomnia, confusion, anxiety, agitation, depressed level of consciousness, nervousness, hallucination, somnolence, depression, suicide

Respiratory System: Bronchospasm, dyspnea, hyperpnea, pulmonary edema, tachypnea, aspiration, hypoventilation, laryngeal edema

Skin and Appendages: Erythema, urticaria, rash, flushing

Urogenital: Interstitial nephritis, papillary necrosis, proteinuria, renal insufficiency and failure, urinary retention

- Serotonin syndrome: Cases of serotonin syndrome, a potentially life-threatening condition, have been reported during concomitant use of opioids with serotonergic drugs.
- Adrenal insufficiency: Cases of adrenal insufficiency have been reported with opioid use, more often following greater than one month of use.
- Anaphylaxis: Anaphylaxis has been reported with ingredients contained in Oxycodone and Acetaminophen Tablets.
- Androgen deficiency: Cases of androgen deficiency have occurred with chronic use of opioids [see CLINICAL PHARMACOLOGY].

To report SUSPECTED ADVERSE REACTIONS, contact AvKARE at 1-855-361-3993; email drugsafety@avkare.com; or FDA at 1-800-FDA-1088 or www.fda.gov/medwatch.

DRUG ABUSE AND DEPENDENCE

Controlled Substance

Oxycodone and Acetaminophen Tablets contain oxycodone, a Schedule II controlled substance.

Abuse

Oxycodone and Acetaminophen Tablets contains oxycodone, a substance with a high potential for abuse similar to other opioids including fentanyl, hydrocodone, hydromorphone, methadone, morphine, oxymorphone, and tapentadol. Oxycodone and Acetaminophen Tablets can be abused and is subject to misuse, addiction, and criminal diversion [see WARNINGS].

All patients treated with opioids require careful monitoring for signs of abuse and addiction, since use of opioid analgesic products carries the risk of addiction even under appropriate medical use.

Prescription drug abuse is the intentional non-therapeutic use of a prescription drug, even once, for its rewarding psychological or physiological effects.

Drug addiction is a cluster of behavioral, cognitive, and physiological phenomena that develop after repeated substance use and includes: a strong desire to take the drug, difficulties in controlling its use, persisting in its use despite harmful consequences, a higher priority given to drug use than to other activities and obligations, increased tolerance, and sometimes a physical withdrawal.

“Drug-seeking” behavior is very common in persons with substance use disorders. Drug-seeking tactics include emergency calls or visits near the end of office hours, refusal to undergo appropriate examination, testing, or referral, repeated “loss” of prescriptions, tampering with prescriptions, and reluctance to provide prior medical records or contact information for other treating health care provider(s). “Doctor shopping” (visiting multiple prescribers to obtain additional prescriptions) is common among drug abusers and people suffering from untreated addiction. Preoccupation with achieving adequate pain relief can be appropriate behavior in a patient with poor pain control.

Abuse and addiction are separate and distinct from physical dependence and tolerance. Health care providers should be aware that addiction may not be accompanied by concurrent tolerance and symptoms of physical dependence in all addicts. In addition, abuse of opioids can occur in the absence of true addiction.

Oxycodone and Acetaminophen Tablets, like other opioids, can be diverted for non-medical use into illicit channels of distribution. Careful record-keeping of prescribing information, including quantity, frequency, and renewal requests, as required by state and federal law, is strongly advised.

Proper assessment of the patient, proper prescribing practices, periodic re-evaluation of therapy, and proper dispensing and storage are appropriate measures that help to limit abuse of opioid drugs.

Risks Specific to Abuse of Oxycodone and Acetaminophen Tablets

Oxycodone and Acetaminophen Tablets are for oral use only. Abuse of Oxycodone and Acetaminophen Tablets poses a risk of overdose and death. The risk is increased with concurrent abuse of Oxycodone and Acetaminophen Tablets with alcohol and other central nervous system depressants.

Acetaminophen has been associated with cases of acute liver failure, at times resulting in liver transplant and death.

Parenteral drug abuse is commonly associated with transmission of infectious diseases such as hepatitis and HIV.

Dependence

Both tolerance and physical dependence can develop during chronic opioid therapy. Tolerance is the need for increasing doses of opioids to maintain a defined effect such as analgesia (in the absence of disease progression or other external factors). Tolerance may occur to both the desired and undesired effects of drugs, and may develop at different rates for different effects.

Physical dependence results in withdrawal symptoms after abrupt discontinuation or a significant dosage reduction of a drug. Withdrawal also may be precipitated through the administration of drugs with opioid antagonist activity (e.g., naloxone, nalmefene), mixed agonist/antagonist analgesics (e.g., pentazocine, butorphanol, nalbuphine), or partial agonists (e.g., buprenorphine). Physical dependence may not occur to a clinically significant degree until after several days to weeks of continued opioid usage.

Oxycodone and Acetaminophen Tablets should not be abruptly discontinued in a physically-dependent patient [see DOSAGE AND ADMINISTRATION]. If Oxycodone and Acetaminophen Tablets is abruptly discontinued in a physically-dependent patient, a withdrawal syndrome may occur. Some or all of the following can characterize this syndrome: restlessness, lacrimation, rhinorrhea, yawning, perspiration, chills, myalgia, and mydriasis. Other signs and symptoms also may develop, including irritability, anxiety, backache, joint pain, weakness, abdominal cramps, insomnia, nausea, anorexia, vomiting, diarrhea, or increased blood pressure, respiratory rate, or heart rate.

Infants born to mothers physically dependent on opioids will also be physically dependent and may exhibit respiratory difficulties and withdrawal signs [see PRECAUTIONS; Pregnancy].

OVERDOSAGE

Following an acute overdosage, toxicity may result from the oxycodone or the acetaminophen.

Clinical Presentation

Acute overdosage with oxycodone can be manifested by respiratory depression, somnolence progressing to stupor or coma, skeletal muscle flaccidity, cold and clammy skin, constricted pupils, and, in some cases, pulmonary edema, bradycardia, hypotension, partial or complete airway obstruction, atypical snoring, and death. Marked mydriasis rather than miosis may be seen with hypoxia in overdose situations.

Acetaminophen

Dose-dependent potentially fatal hepatic necrosis is the most serious adverse effect of acetaminophen overdosage. Renal tubular necrosis, hypoglycemic coma, and coagulation defects may also occur.

Early symptoms following a potentially hepatotoxic overdose may include: nausea, vomiting, diaphoresis, and general malaise. Clinical and laboratory evidence of hepatic toxicity may not be apparent until 48 to 72 hours post-ingestion.

Treatment of Overdose

Oxycodone

In case of overdose, priorities are the reestablishment of a patent and protected airway and institution of assisted or controlled ventilation, if needed. Employ other supportive measures (including oxygen and vasopressors) in the management of circulatory shock and pulmonary edema as indicated. Cardiac arrest or arrhythmias will require advanced life-support techniques.

The opioid antagonists, naloxone or nalmefene, are specific antidotes to respiratory depression resulting from opioid overdose. For clinically significant respiratory or circulatory depression secondary to oxycodone overdose, administer an opioid antagonist. Opioid antagonists should not be administered in the absence of clinically significant respiratory or circulatory depression secondary to oxycodone overdose.

Because the duration of opioid reversal is expected to be less than the duration of action of oxycodone in Oxycodone and Acetaminophen Tablets, carefully monitor the patient until spontaneous respiration is reliably reestablished. If the response to an opioid antagonist is suboptimal or only brief in nature, administer additional antagonist as directed by the product’s prescribing information.

In an individual physically dependent on opioids, administration of the recommended usual dosage of the antagonist will precipitate an acute withdrawal syndrome. The severity of the withdrawal symptoms experienced will depend on the degree of physical dependence and the dose of the antagonist administered. If a decision is made to treat serious respiratory depression in the physically dependent patient, administration of the antagonist should be initiated with care and by titration with smaller than usual doses of the antagonist.

Acetaminophen

Gastric decontamination with activated charcoal should be administered just prior to N-acetylcysteine (NAC) to decrease systemic absorption if acetaminophen ingestion is known or suspected to have occurred within a few hours of presentation. Serum acetaminophen levels should be obtained immediately if the patient presents 4 hours or more after ingestion to assess potential risk of hepatotoxicity; acetaminophen levels drawn less than 4 hours post-ingestion may be misleading. To obtain the best possible outcome, NAC should be administered as soon as possible where impending or evolving liver injury is suspected. Intravenous NAC may be administered when circumstances preclude oral administration.

Vigorous supportive therapy is required in severe intoxication. Procedures to limit the continuing absorption of the drug must be readily performed since the hepatic injury is dose dependent and occurs early in the course of intoxication.

DOSAGE AND ADMINISTRATION

Important Dosage and Administration Instructions

Use the lowest effective dosage for the shortest duration consistent with individual patient treatment goals [see WARNINGS].

Initiate the dosing regimen for each patient individually, taking into account the patient's severity of pain, patient response, prior analgesic treatment experience, and risk factors for addiction, abuse, and misuse [see WARNINGS].

Monitor patients closely for respiratory depression, especially within the first 24 to 72 hours of initiating therapy and following dosage increases with Oxycodone and Acetaminophen Tablets and adjust the dosage accordingly [see WARNINGS].

Patient Access to Naloxone for the Emergency Treatment of Opioid Overdose
Discuss the availability of naloxone for the emergency treatment of opioid overdose with the patient and caregiver and assess the
potential need for access to naloxone, both when initiating and renewing treatment with Oxycodone and Acetaminophen Tablets [see WARNINGS, LifeThreatening Respiratory Depression; PRECAUTIONS, Information for Patients/Caregivers].

Inform patients and caregivers about the various ways to obtain naloxone as permitted by individual state naloxone dispensing and
prescribing regulations (e.g., by prescription, directly from a pharmacist, or as part of a community-based program).

Consider prescribing naloxone, based on the patient’s risk factors for overdose, such as concomitant use of CNS depressants, a history of opioid use disorder, or prior opioid overdose. The presence of risk factors for overdose should not prevent the proper management of pain in any given patient [see WARNINGS, Addiction, Abuse, and Misuse, LifeThreatening Respiratory Depression, and Risks from Concomitant Use with Benzodiazepines or Other CNS Depressants].

Consider prescribing naloxone when the patient has household members (including children) or other close contacts at risk for
accidental ingestion or overdose.

Initial Dosage

Initiating Treatment with Oxycodone and Acetaminophen Tablets

The usual adult dosage is one tablet every 6 hours as needed for pain. The total daily dose of acetaminophen should not exceed 4 grams.

Strength | Usual Adult Dosage | Maximal Daily Dose
Oxycodone and Acetaminophen Tablets 5 mg/325 mg | 1 tablet every 6 hours as needed for pain | 12 Tablets
Oxycodone and Acetaminophen Tablets 7.5 mg/ 325 mg | 1 tablet every 6 hours as needed for pain | 8 Tablets
Oxycodone and Acetaminophen Tablets 10 mg/325 mg | 1 tablet every 6 hours as needed for pain | 6 Tablets

Conversion from Oxycodone and Acetaminophen to Extended-Release Oxycodone

The relative bioavailability of Oxycodone and Acetaminophen Tablets compared to extended-release oxycodone is unknown, so conversion to extended-release oxycodone must be accompanied by close observation for signs of excessive sedation and respiratory depression.

Titration and Maintenance of Therapy

Individually titrate Oxycodone and Acetaminophen Tablets to a dose that provides adequate analgesia and minimizes adverse reactions. Continually reevaluate patients receiving Oxycodone and Acetaminophen Tablets to assess the maintenance of pain control and the relative incidence of adverse reactions, as well as monitoring for the development of addiction, abuse, or misuse [see WARNINGS]. Frequent communication is important among the prescriber, other members of the healthcare team, the patient, and the caregiver/family during periods of changing analgesic requirements, including initial titration.

If the level of pain increases after dosage stabilization, attempt to identify the source of increased pain before increasing the Oxycodone and Acetaminophen Tablets dosage. If unacceptable opioid-related adverse reactions are observed, consider reducing the dosage. Adjust the dosage to obtain an appropriate balance between management of pain and opioid-related adverse reactions.

Discontinuation of Oxycodone and Acetaminophen Tablets

When a patient who has been taking Oxycodone and Acetaminophen Tablets regularly and may be physically dependent no longer requires therapy with Oxycodone and Acetaminophen Tablets, use a gradual downward titration of the dosage to prevent signs and symptoms of withdrawal. Do not stop Oxycodone and Acetaminophen Tablets abruptly [see WARNINGS, DRUG ABUSE AND DEPENDENCE].

HOW SUPPLIED

Oxycodone and Acetaminophen Tablets, USP, 5 mg/325 mg are supplied as white to off-white, round, flat-faced, beveled edged tablets, debossed “IP203” on obverse and bisect on reverse.

They are available as follows:

NDC 50268-644-15 (10 tablets per card, 5 cards per carton)

Oxycodone and Acetaminophen Tablets, USP, 7.5 mg/325 mg are supplied as white to off-white, capsule-shaped, biconvex tablets, debossed “IP207” on obverse and plain on the reverse.

They are available as follows:

NDC 50268-645-15 (10 Tablets per card, 5 cards per carton).

Oxycodone and Acetaminophen Tablets, USP, 10 mg/325 mg are supplied as white to off-white, capsule-shaped, biconvex tablets, debossed “IP204” on obverse and plain on reverse.

They are available as follows:

NDC 50268-646-15 (10 Tablets per card, 5 cards per carton).

Dispensed in Unit Dose Package. For Institution Use Only.

Storage

Store at 20° to 25°C (68° to 77°F) [see USP Controlled Room Temperature]. Protect from moisture.

Manufactured for:
AvKARE
Pulaski, TN 38478
AvPAK
Mfg. Rev. 10-2021-11
AV Rev. 11/23 (M)

Medication Guide

Oxycodone (ox” I koe’ done) and Acetaminophen (a seet” a min’ oh fen) Tablets CII

Oxycodone and Acetaminophen Tablets are:

- A strong prescription pain medicine that contains an opioid (narcotic) that is used to manage pain, severe enough to require an opioid analgesic and for which alternative treatments are inadequate and when other pain treatments such as non-opioid pain medicines do not treat your pain well enough or you cannot tolerate them.
- An opioid pain medicine that can put you at risk for overdose and death. Even if you take your dose correctly as prescribed you are at risk for opioid addiction, abuse, and misuse that can lead to death.

Important information about Oxycodone and Acetaminophen Tablets:

- Get emergency help right away if you take too much Oxycodone and Acetaminophen Tablets (overdose). When you first start taking Oxycodone and Acetaminophen Tablets, when your dose is changed, or if you take too much (overdose), serious or life-threatening breathing problems that can lead to death may occur.
- Taking Oxycodone and Acetaminophen Tablets with other opioid medicines, benzodiazepines, alcohol, or other central nervous system depressants (including street drugs) can cause severe drowsiness, decreased awareness, breathing problems, coma, and death.
- Never give anyone else your Oxycodone and Acetaminophen Tablets. They could die from taking it. Store Oxycodone and Acetaminophen Tablets away from children and in a safe place to prevent stealing or abuse. Selling or giving away Oxycodone and Acetaminophen Tablets are against the law.
- Store Oxycodone and Acetaminophen Tablets securely, out of sight and reach of children, and in a location not accessible by others, including visitors to the home.

Do not take Oxycodone and Acetaminophen Tablets if you have:

- Severe asthma, trouble breathing, or other lung problems.
- A bowel blockage or have narrowing of the stomach or intestines.
- Known hypersensitivity to oxycodone, acetaminophen, or any ingredient in Oxycodone and Acetaminophen Tablets.

Before taking Oxycodone and Acetaminophen Tablets, tell your healthcare provider if you have a history of:

- Head injury, seizures
- Liver, kidney, thyroid problems
- Problems urinating
- Pancreas or gallbladder problems
- Abuse of street or prescription drugs, alcohol addiction, or mental health problems

Tell your healthcare provider if you are:

- Pregnant or planning to become pregnant. Prolonged use of Oxycodone and Acetaminophen Tablets during pregnancy can cause withdrawal symptoms in your newborn baby that could be life-threatening if not recognized and treated.
- Breastfeeding. Oxycodone and Acetaminophen Tablets passes into breast milk and may harm your baby.
- Taking prescription or over-the-counter medicines, vitamins, or herbal supplements. Taking Oxycodone and Acetaminophen Tablets with certain other medicines can cause serious side effects that could lead to death.

When taking Oxycodone and Acetaminophen Tablets:

- Do not change your dose. Take Oxycodone and Acetaminophen Tablets exactly as prescribed by your healthcare provider. Use the lowest dose possible for the shortest time needed.
- Take your prescribed dose every 6 hours as needed for pain. Do not take more than your prescribed dose. If you miss a dose, take your next dose at your usual time.
- Call your healthcare provider if the dose you are taking does not control your pain.
- If you have been taking Oxycodone and Acetaminophen Tablets regularly, do not stop taking Oxycodone and Acetaminophen Tablets without talking to your healthcare provider.
- Dispose of expired, unwanted, or unused Oxycodone and Acetaminophen Tablets by promptly flushing down the toilet, if a drug take-back option is not readily available. Visit www.fda.gov/drugdisposal for additional information on disposal of unused medicines.

While taking Oxycodone and Acetaminophen Tablets DO NOT:

- Drive or operate heavy machinery, until you know how Oxycodone and Acetaminophen Tablets affects you. Oxycodone and Acetaminophen Tablets can make you sleepy, dizzy, or lightheaded.
- Drink alcohol or use prescription or over-the-counter medicines that contain alcohol. Using products containing alcohol during treatment with Oxycodone and Acetaminophen Tablets may cause you to overdose and die.

The possible side effects of Oxycodone and Acetaminophen Tablets:

- Constipation, nausea, sleepiness, vomiting, tiredness, headache, dizziness, abdominal pain. Call your healthcare provider if you have any of these symptoms and they are severe.

Get emergency medical help if you have:

- Trouble breathing, shortness of breath, fast heartbeat, chest pain, swelling of your face, tongue, or throat, extreme drowsiness, light-headedness when changing positions, feeling faint, agitation, high body temperature, trouble walking, stiff muscles, or mental changes such as confusion.

These are not all the possible side effects of Oxycodone and Acetaminophen Tablets. Call your doctor for medical advice about side effects. You may report side effects to FDA at 1-800-FDA-1088. For more information go to dailymed.nlm.nih.gov

Manufactured for:
AvKARE
Pulaski, TN 38478
Mfg. Rev. 10-2021-07
AV Rev. 11/23 (M)

This Medication Guide has been approved by the U.S. Food and Drug Administration.